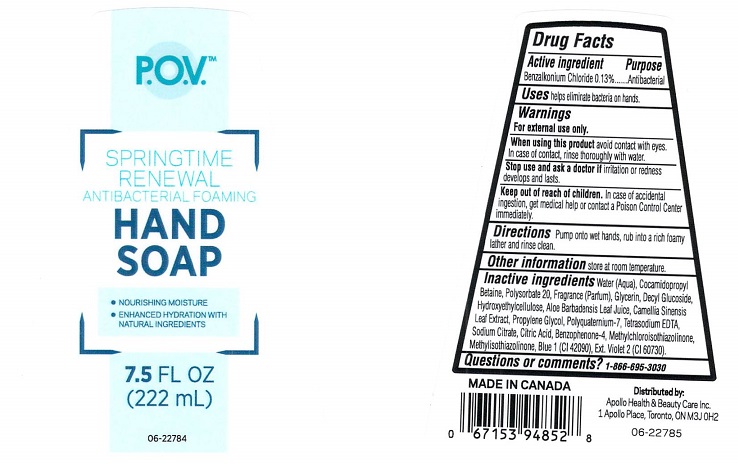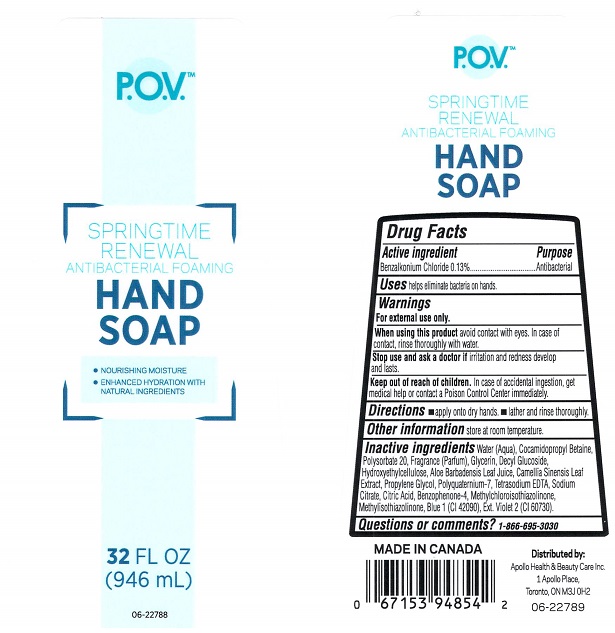 DRUG LABEL: P.O.V. Springtime Renewal Antibacterial Foaming Hand
NDC: 63148-198 | Form: SOAP
Manufacturer: Apollo Health and Beauty Care Inc.
Category: otc | Type: HUMAN OTC DRUG LABEL
Date: 20171113

ACTIVE INGREDIENTS: BENZALKONIUM CHLORIDE 1.3 mg/1 mL
INACTIVE INGREDIENTS: WATER; COCAMIDOPROPYL BETAINE; POLYSORBATE 20; GLYCERIN; DECYL GLUCOSIDE; HYDROXYETHYL CELLULOSE (5000 CPS AT 1%); ALOE VERA LEAF; GREEN TEA LEAF; PROPYLENE GLYCOL; POLYQUATERNIUM-7 (70/30 ACRYLAMIDE/DADMAC; 1600000 MW); EDETATE SODIUM; SODIUM CITRATE; CITRIC ACID MONOHYDRATE; SULISOBENZONE; METHYLCHLOROISOTHIAZOLINONE; METHYLISOTHIAZOLINONE; FD&C BLUE NO. 1; EXT. D&C VIOLET NO. 2

Drug Facts

Active ingredient

Benzalkonium Chloride 0.13%

Purpose

Antibacterial

Uses

helps eliminate bacteria on hands.

Warnings

For external use only.

When using this product

avoid contact with eyes. In case of contact, rinse thoroughly with water.

Stop use and ask a doctor if

irritation and redness develops and lasts.

Keep out of reach of children.

In case of accidental ingestion, get medical help or contact a Poison Control Center immediately.

Directions

- apply onto dry hands.
- lather and rinse thoroughly.

Other information

store at room temperature.

Inactive ingredients

Water (Aqua), Cocamidopropyl Betaine, Polysorbate 20, Fragrance (Parfum), Glycerin, Decyl Glucoside Hydroxyethylcelluose, Aloe Barbadensis Leaf Juice, Camellia Sinensis Leaf Extract, Propylen Glycol, Polyquaternium-7, Tetrasodium EDTA, Sodium Citrate, Citric Acid, Benzophenone-4, Methylchloroisothiazolinone, Methylisothiazolinone, Blue 1 (CI 42090), Ext. Violet 2 (CI 60730).

Questions or comments?

1-866-695-3030